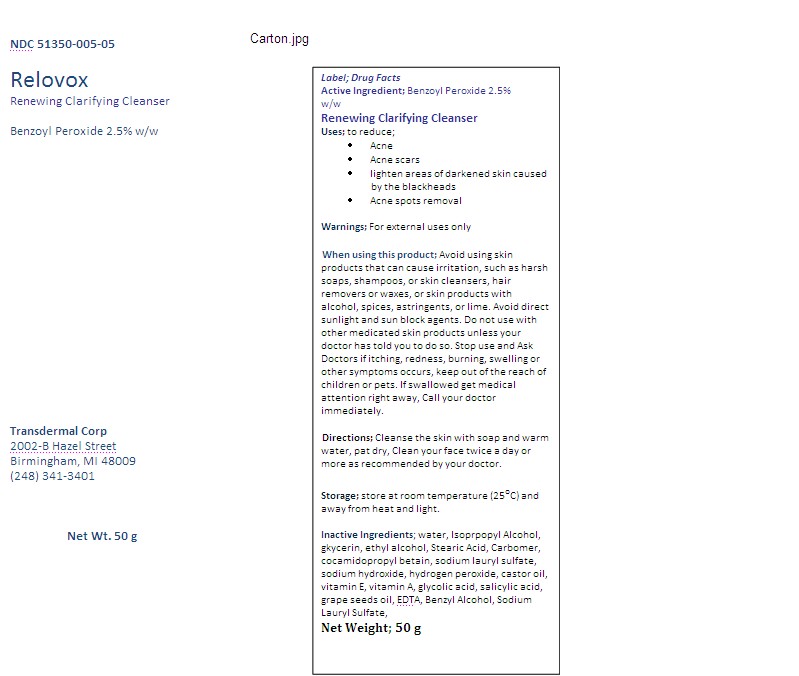 DRUG LABEL: Relovox
NDC: 51350-005 | Form: EMULSION
Manufacturer: Transdermal Corp
Category: otc | Type: HUMAN OTC DRUG LABEL
Date: 20110331

ACTIVE INGREDIENTS: BENZOYL PEROXIDE 25 mg/1 g
INACTIVE INGREDIENTS: WATER; CARBOMER HOMOPOLYMER TYPE C; GLYCERIN; STEARIC ACID; SODIUM LAURYL SULFATE; ISOPROPYL ALCOHOL; ZINC ACETATE; ALCOHOL; ALOE ; COCAMIDOPROPYL BETAINE; GLYCOLIC ACID; BUTYLENE GLYCOL; CASTOR OIL; SODIUM HYDROXIDE; SALICYL ALCOHOL; SALICYLIC ACID; VITAMIN A PALMITATE

Drug Facts

Active Ingredient; Benzoyl Peroxide 2.5% (w/w)

DOSAGE AND ADMINISTRATION

Apply on the skin with a gentle massage twice a day, rinse thoroughly with hot water, pat dry with a clean towel. Children under 2 years of age, consult your doctor

PURPOSE

Use for the management of acne and pimples and acne spots removal.

INDICATIONS AND USAGE

Indicated and use for the management of acne and removal of the acne spots, Apply on the skin with a gentle massage twice a day, rinse thoroughly with hot water, pat dry with a clean towel.Children under 2 years of age, consult your doctor

Keep out of reach of children, store in a cool dry place at room temperature.

INACTIVE INGREDIENT

Inactive Ingredients; water, Isoprpopyl Alcohol, glycerin, ethyl alcohol, staeric acid, carbomer, sodium hydroxide, cocamidopropyl betain, sodium lauryl sulfate, castor oil,glycolic acid, salicylic acid, cocoa butter, vitamin E, vitamin A, grape seeds oil.

DO NOT USE

• Ask your doctor if you using other acne medications
• Do not use if you are allergic to Benzoyl Peroxide
• Do not use in or near the eyes
• Do not use in large amount particularly over the raw surfaces or blisters
Stop use and Ask Doctors if
• Allergic reactions occurs
• Condition worsen and does not improve
• Excessive dryness and peeling of skin occurs
• itching, redness, burning , swelling or other symptoms occurs
• Keep both used and unused medicine out of the reach of children or pets
• If swallowed get medical attention right away Call your doctor immediately.

• Do not use in or near the eyes
• Do not use in large amount particularly over the raw surfaces or blisters
Stop use and Ask Doctors if
• Allergic reactions occurs
• Condition worsen and does not improve

PACKAGE LABEL

carton.jpg